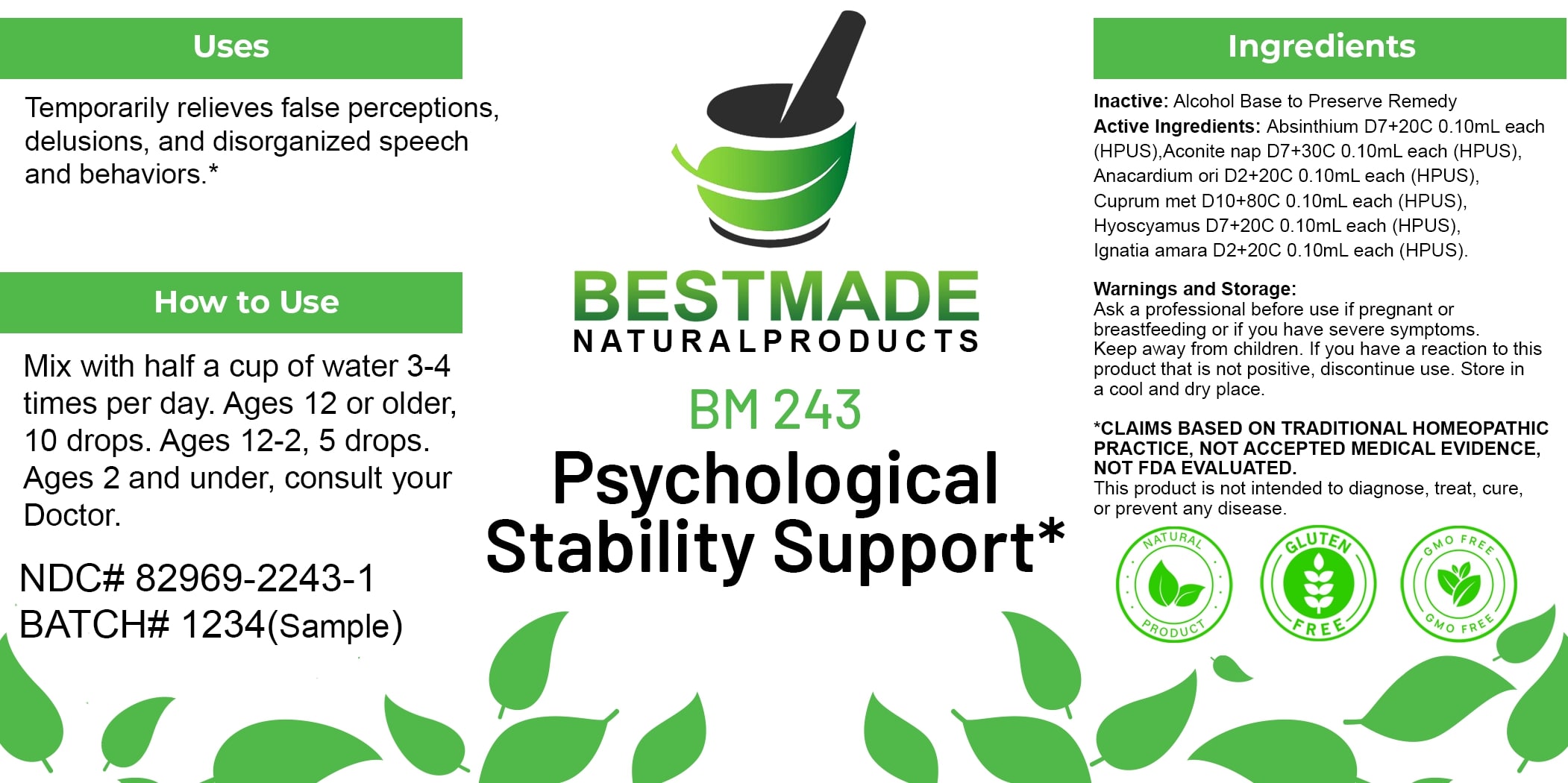 DRUG LABEL: Bestmade Natural Products BM243
NDC: 82969-2243 | Form: LIQUID
Manufacturer: Bestmade Natural Products
Category: homeopathic | Type: HUMAN OTC DRUG LABEL
Date: 20250304

ACTIVE INGREDIENTS: HYOSCYAMUS NIGER 30 [hp_C]/30 [hp_C]; STRYCHNOS IGNATII SEED 30 [hp_C]/30 [hp_C]; ACONITUM NAPELLUS 30 [hp_C]/30 [hp_C]; COPPER 30 [hp_C]/30 [hp_C]; SEMECARPUS ANACARDIUM JUICE 30 [hp_C]/30 [hp_C]; WORMWOOD 30 [hp_C]/30 [hp_C]
INACTIVE INGREDIENTS: ALCOHOL 30 [hp_C]/30 [hp_C]

BM243

DOSAGE AND ADMINISTRATION

How to Use

Mix with half a cup of water 3-4 times per day. Ages 12 or older, 10 drops. Ages 12-2, 5 drops. Ages 2 and under, consult your Doctor.

Uses

Temporarily relieves false perceptions, delusions, and disorganized speech and behaviors.*

*CLAIMS BASED ON TRADITIONAL HOMEOPATHIC PRACTICE, NOT ACCEPTED MEDICAL EVIDENCE, NOT FDA EVALUATED.

This product is not intended to diagnose, treat, cure, or prevent any disease.

INACTIVE INGREDIENT

Ingredients

Inactive: Alcohol Base to Preserve Remedy

ACTIVE INGREDIENT

Active Ingredients: Absinthium D7+20C 0.10mL each (HPUS), Aconite nap D7+30C 0.10mL each (HPUS), Anacardium ori D2+20C 0.10mL each (HPUS), Cuprum met D10+80C 0.10mL each (HPUS), Hyoscyamus D7+20C 0.10mL each (HPUS), Ignatia amara D2+20C 0.10mL each (HPUS).

KEEP OUT OF REACH OF CHILDREN

Warnings and Storage:

Ask a professional before use if pregnant or breastfeeding or if you have severe symptoms. Keep away from children. If you have a reaction to this product that is not positive, discontinue use. Store in a cool and dry place.

Warnings and Storage:

Ask a professional before use if pregnant or breastfeeding or if you have severe symptoms. Keep away from children. If you have a reaction to this product that is not positive, discontinue use. Store in a cool and dry place.

*CLAIMS BASED ON TRADITIONAL HOMEOPATHIC PRACTICE, NOT ACCEPTED MEDICAL EVIDENCE, NOT FDA EVALUATED.

This product is not intended to diagnose, treat, cure, or prevent any disease.

Uses

Temporarily relieves false perceptions, delusions, and disorganized speech and behaviors.*

*CLAIMS BASED ON TRADITIONAL HOMEOPATHIC PRACTICE, NOT ACCEPTED MEDICAL EVIDENCE, NOT FDA EVALUATED.

This product is not intended to diagnose, treat, cure, or prevent any disease.

Entire package label